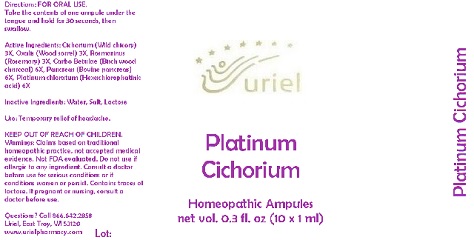 DRUG LABEL: Platinum Cichorium
NDC: 48951-8042 | Form: LIQUID
Manufacturer: Uriel Pharmacy Inc.
Category: homeopathic | Type: HUMAN OTC DRUG LABEL
Date: 20170803

ACTIVE INGREDIENTS: CICHORIUM INTYBUS WHOLE 3 [hp_X]/1 mL; OXALIS ACETOSELLA LEAF 3 [hp_X]/1 mL; ROSMARINUS OFFICINALIS FLOWERING TOP 3 [hp_X]/1 mL; ACTIVATED CHARCOAL 6 [hp_X]/1 mL; SUS SCROFA PANCREAS 6 [hp_X]/1 mL; PLATINUM 6 [hp_X]/1 mL
INACTIVE INGREDIENTS: WATER; SODIUM CHLORIDE; LACTOSE

Platinum Cichorium

INDICATIONS AND USAGE

Directions: FOR ORAL USE.

DOSAGE AND ADMINISTRATION

Take the contents of one ampule under the tongue and hold for 30 seconds, then swallow.

ACTIVE INGREDIENT

Active Ingredients: Cichorium (Wild chicory) 3X, Oxalis (Wood sorrel) 3X, Rosmarinus (Rosemary) 3X, Carbo Betulae (Birch wood charcoal) 6X, Pancreas (Bovine pancreas) 6X, Platinum chloratum (Hexachlorophatinic acid) 6X

Inactive Ingredients: Water, Salt, Lactose

PURPOSE

Use: Temporary relief of headache.

KEEP OUT OF REACH OF CHILDREN.

WARNINGS

Warnings: Claims based on traditional homeopathic practice, not accepted medical evidence. Not FDA evaluated. Do not use if allergic to any ingredient. Consult a doctor before use for serious conditions or if conditions worsen or persist. Contains traces of lactose. If pregnant or nursing, consult a doctor before use.

QUESTIONS

Questions? Call 866.642.2858 Uriel, East Troy, WI 53120 www.urielpharmacy.com